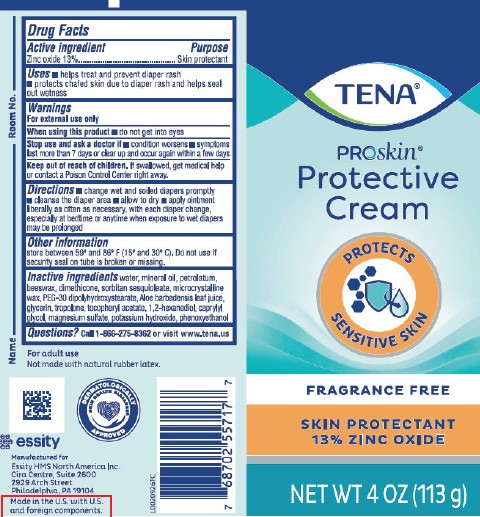 DRUG LABEL: TENA Proskin protective cream
NDC: 59608-017 | Form: CREAM
Manufacturer: Essity Professional Hygiene North America LLC 
Category: otc | Type: HUMAN OTC DRUG LABEL
Date: 20260204

ACTIVE INGREDIENTS: ZINC OXIDE 130 mg/1 g
INACTIVE INGREDIENTS: WATER; MINERAL OIL; PETROLATUM; YELLOW WAX; DIMETHICONE; SORBITAN SESQUIOLEATE; MICROCRYSTALLINE WAX; PEG-30 DIPOLYHYDROXYSTEARATE; ALOE VERA LEAF; GLYCERIN; TROPOLONE; .ALPHA.-TOCOPHEROL ACETATE; 1,2-HEXANEDIOL; CAPRYLYL GLYCOL; MAGNESIUM SULFATE, UNSPECIFIED FORM; POTASSIUM HYDROXIDE; PHENOXYETHANOL

Tena_Essity 226.002/226AD
Creamy Diaper Rash Ointment

Active ingredient

Zinc oxide 13%

Purpose

Skin protectant

Uses

- helps treat and prevent diaper rash
- protects chafed skin due to diaper rash and helps seal out wetness

Warnings

For external use only

When using this product

- do not get into eyes

Stop use and ask a doctor if

- condition worsens
- symptoms last more than 7 days or clear up and occur again within a few days

Keep out of reach of children.

If swallowed, get medical help or contact a Poison Control Center right away.

Directions

- change wet and soiled diapers promptly
- cleanse the diaper area
- allow to dry
- apply ointment liberally as often as necessary, with each diaper change, especially at bedtime or anytime when exposure to wet diapers may be prolonged

Other information

store between 59º and 86º F (15º and 30º C). Do not use if security seal on tube is broken or missing.

Inactive ingredients

water, mineral oil, petrolatum, beeswax, dimethicone, sorbitan sesquioleate, microcrystalline wax, PEG-30 dipolyhydroxystearate, Aloe barbadensis leaf juice, glycerin, tropolone, tocopheryl acetate, 1,2-hexanediol, caprylyl glycol, magnesium sulfate, potassium hydroxide, phenoxyethanol

Questions?

Call 1-866-275-8362 or visit www.tena.us

Claims

For adult use

Not made with natural rubber latex.

DERMATOLOGICALLY APPROVED

essity

Made in the U.S. with U.S. and foreign components.

Adverse reaction

Manufactured for

Essity HMS North America Inc.

Cira Centre, Suite 2600

2929 Arch Street

Philadelphia, PA 19104

Principal Panel Display

TENA®

Proskin®

Protective Cream

Protects Sensitive Skin

Fragrance Free

Skin Protectant

13% Zinc Oxide

Net WT 4 OZ (113 g)